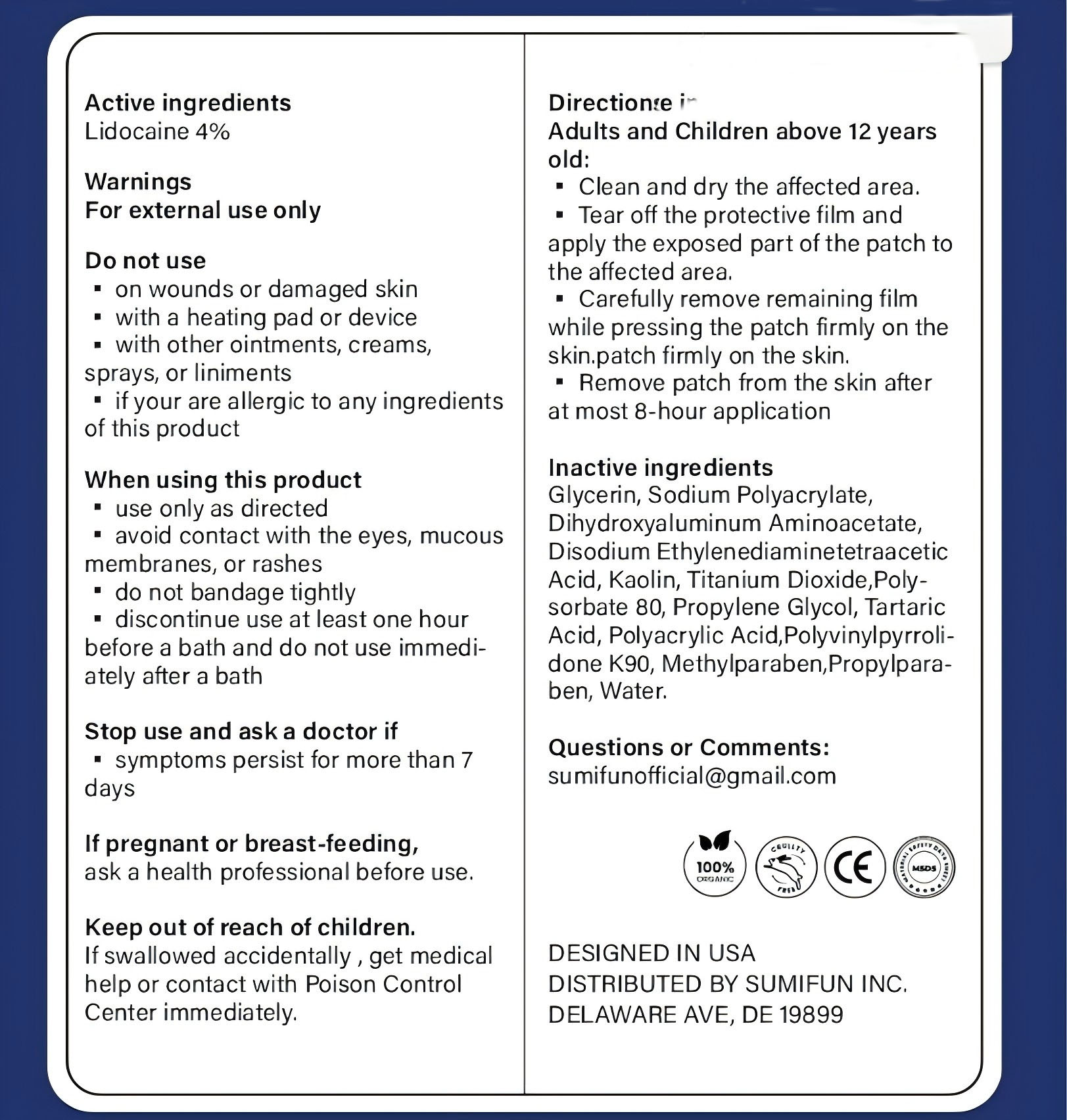 DRUG LABEL: Lidocaine Pain Relief Gel-Patch
NDC: 84732-082 | Form: PATCH
Manufacturer: Dongguan Haiyi Technology Co.,Ltd.
Category: otc | Type: HUMAN OTC DRUG LABEL
Date: 20241104

ACTIVE INGREDIENTS: LIDOCAINE 4 mg/100 g
INACTIVE INGREDIENTS: PROPYLENE GLYCOL; DIHYDROXYALUMINUM AMINOACETATE; PROPYLPARABEN; TITANIUM DIOXIDE; GLYCERIN; TARTARIC ACID; POLYACRYLIC ACID (250000 MW); POVIDONE K90; METHYLPARABEN; MAGNESIUM DISODIUM EDTA; SODIUM POLYACRYLATE (2500000 MW); KAOLIN; WATER; POLYSORBATE 80

Active ingredients

Lidocaine 4%

Inactive ingredients

Glycerin, Sodium Polyacrylate,Dihydroxyaluminum Aminoacetate,Disodium EthylenediaminetetraaceticAcid, Kaolin, Titanium Dioxide,Poly-sorbate 80, Propylene Glycol, TartaricAcid, Polyacrylic Acid,Polyvinylpyrroli-done K90, Methylparaben,Propylpara-ben, Water.

Purpose section

Desensitizes AggravatedNerves And Relieves Pain :

No lrritation

Stay-put Flexible Patch

Numbs Pain Away

Warning

For external use only

stop use

on wounds or damaged skin

with a heating pad or devic

with other ointments, creams,sprays, or liniments

if your are allergic to any ingredients of this product

not use

Not suitable for use by children, pregnantor breast feeding people.

Keep out of reach of children.

If swallowed accidentally , get medical help or contact with Poison Control Center immediately.

HOW TO USE

Adults and Children above 12 year sold:
Clean and dry the affected area.

Tear off the protective film andapply the exposed part of the patch tothe affected area.

Carefully remove remaining film while pressing the patch firmly on theskin.patch firmly on the skin.

Remove patch from the skin afterat most 8-hour application

Dosage

take an appropriateamount,Use 2-3 times a week